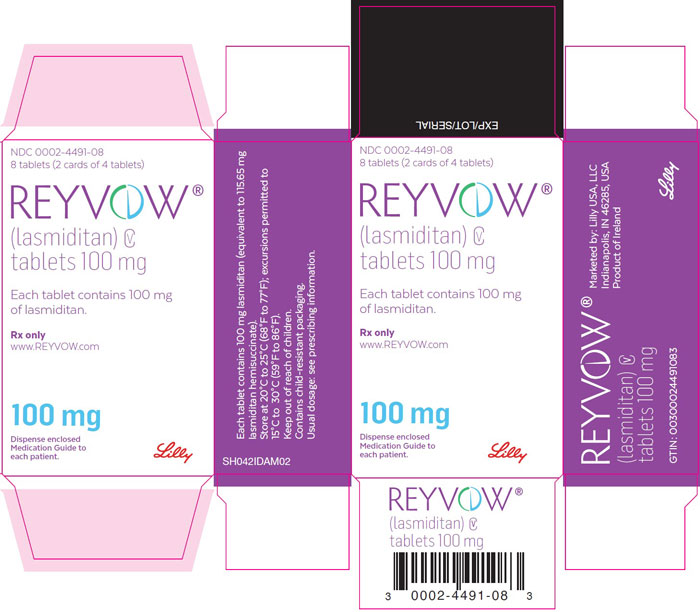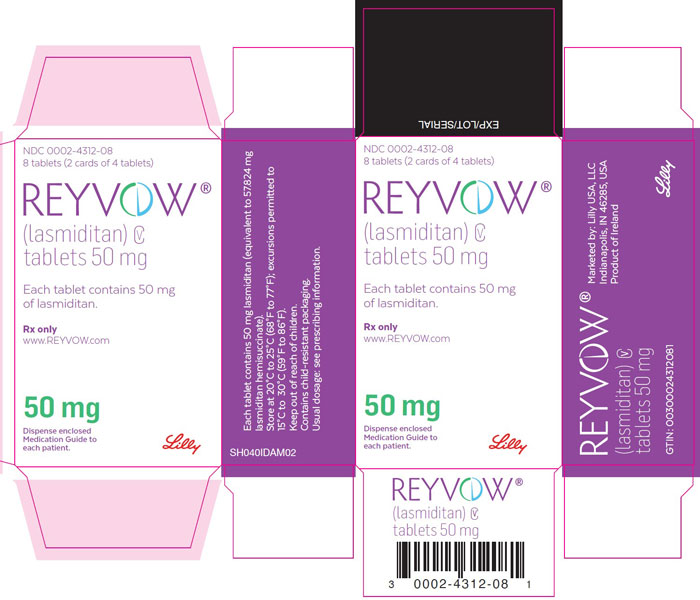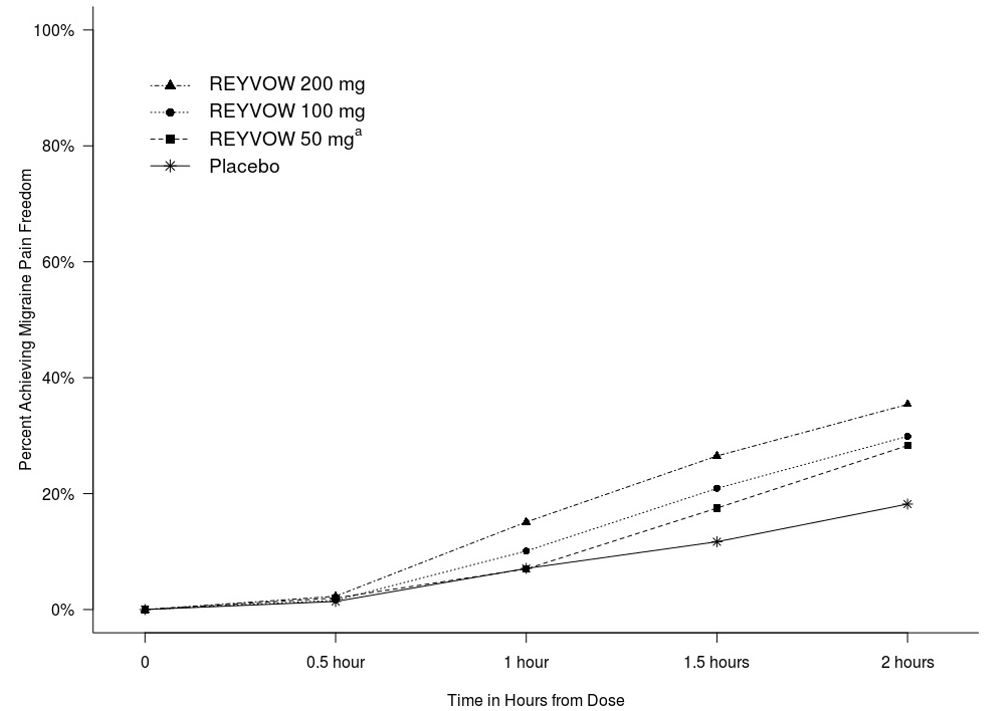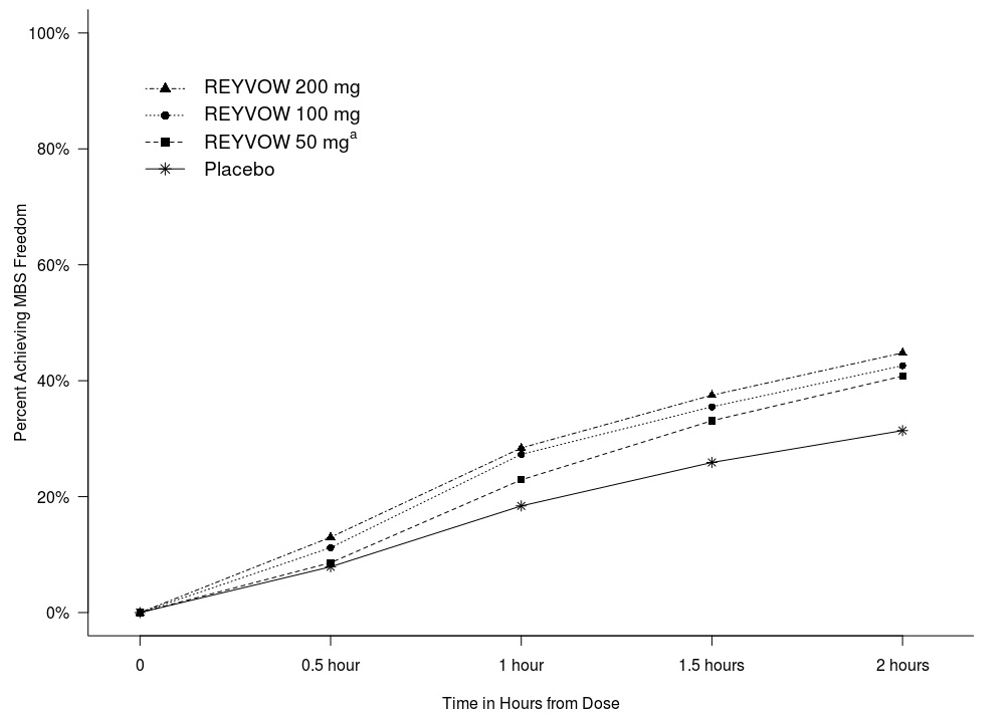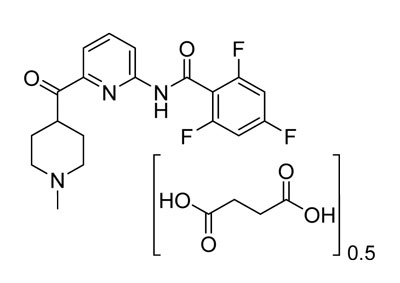 DRUG LABEL: Reyvow
NDC: 0002-4312 | Form: TABLET
Manufacturer: Eli Lilly and Company
Category: prescription | Type: HUMAN PRESCRIPTION DRUG LABEL
Date: 20241113
DEA Schedule: CV

ACTIVE INGREDIENTS: lasmiditan 50 mg/1 1
INACTIVE INGREDIENTS: Microcrystalline cellulose; Starch, corn; Croscarmellose Sodium; Sodium Lauryl Sulfate; Magnesium Stearate; Polyvinyl Alcohol, Unspecified; Titanium dioxide; Polyethylene Glycol 3350; Talc; Ferrosoferric Oxide

HIGHLIGHTS OF PRESCRIBING INFORMATION

These highlights do not include all the information needed to use REYVOW safely and effectively. See full prescribing information for REYVOW.
REYVOW (lasmiditan) tablets, for oral use, CV
Initial U.S. Approval: 2020

1 INDICATIONS AND USAGE

REYVOW® is a serotonin (5-HT) 1F receptor agonist indicated for the acute treatment of migraine with or without aura in adults. (1)

Limitations of Use

REYVOW is not indicated for the preventive treatment of migraine. (1)

2 DOSAGE AND ADMINISTRATION

- The recommended dose is 50 mg, 100 mg, or 200 mg taken orally, as needed. (2)
- No more than one dose should be taken in 24 hours. (2, 5.1)
- Administer tablets whole. (2)

3 DOSAGE FORMS AND STRENGTHS

Tablets: 50 mg, 100 mg (3)

4 CONTRAINDICATIONS

- None. (4)

5 WARNINGS AND PRECAUTIONS

- Driving Impairment: Advise patients not to drive or operate machinery until at least 8 hours after taking each dose of REYVOW. Patients who cannot follow this advice should not take REYVOW. Patients may not be able to assess their own driving competence and the degree of impairment caused by REYVOW. (5.1)
- Central Nervous System (CNS) Depression: REYVOW may cause CNS depression and should be used with caution if used in combination with alcohol or other CNS depressants. (5.2, 7.1)
- Serotonin Syndrome: Reactions consistent with serotonin syndrome were reported in patients treated with REYVOW. Discontinue REYVOW if symptoms of serotonin syndrome occur. (5.3)
- Medication Overuse Headache: Detoxification may be necessary. (5.4)

6 ADVERSE REACTIONS

Most common adverse reactions (≥5% and > placebo) were dizziness, fatigue, paresthesia, and sedation. (6.1)

To report SUSPECTED ADVERSE REACTIONS, contact Eli Lilly and Company at 1-800-LillyRx (1-800-545-5979) or FDA at 1-800-FDA-1088 or www.fda.gov/medwatch.

7 DRUG INTERACTIONS

- REYVOW may further lower heart rate when administered with heart rate lowering drugs. (7.3)

8 USE IN SPECIFIC POPULATIONS

- Based on animal data, may cause fetal harm. (8.1)
- REYVOW has not been studied in patients with severe hepatic impairment (Child-Pugh C) and its use in these patients is not recommended. (8.6)

FULL PRESCRIBING INFORMATION

1 INDICATIONS AND USAGE

REYVOW® is indicated for the acute treatment of migraine with or without aura in adults.

Limitations of Use

REYVOW is not indicated for the preventive treatment of migraine.

2 DOSAGE AND ADMINISTRATION

The recommended dose of REYVOW is 50 mg, 100 mg, or 200 mg taken orally, as needed. No more than one dose should be taken in 24 hours, and REYVOW should not be taken unless the patient can wait at least 8 hours between dosing and driving or operating machinery [see Warnings and Precautions (5.1)].

A second dose of REYVOW has not been shown to be effective for the same migraine attack.

The safety of treating an average of more than 4 migraine attacks in a 30-day period has not been established.

REYVOW may be taken with or without food.

Administer tablets whole; do not split, crush, or chew.

3 DOSAGE FORMS AND STRENGTHS

REYVOW (lasmiditan) tablets are available in two strengths:

- 50 mg tablet: light gray, oval, film coated, tablets with “L-50” debossed on one side and “4312” on the other
- 100 mg tablet: light purple, oval, film coated, tablets with “L-100” debossed on one side and “4491” on the other

4 CONTRAINDICATIONS

None.

5 WARNINGS AND PRECAUTIONS

5.1 Driving Impairment

REYVOW may cause significant driving impairment. In a driving study, administration of single 50 mg, 100 mg, or 200 mg doses of REYVOW significantly impaired subjects' ability to drive [see Clinical Studies (14.2)]. Additionally, more sleepiness was reported at 8 hours following a single dose of REYVOW compared to placebo. Advise patients not to engage in potentially hazardous activities requiring complete mental alertness, such as driving a motor vehicle or operating machinery, for at least 8 hours after each dose of REYVOW. Patients who cannot follow this advice should not take REYVOW. Prescribers and patients should be aware that patients may not be able to assess their own driving competence and the degree of impairment caused by REYVOW.

5.2 Central Nervous System Depression

REYVOW may cause central nervous system (CNS) depression, including dizziness and sedation [see Adverse Reactions (6.1)].

Because of the potential for REYVOW to cause sedation, other cognitive and/or neuropsychiatric adverse reactions, and driving impairment, REYVOW should be used with caution if used in combination with alcohol or other CNS depressants [see Drug Interactions (7.1)]. Patients should be warned against driving and other activities requiring complete mental alertness for at least 8 hours after REYVOW is taken [see Warnings and Precautions (5.1)].

5.3 Serotonin Syndrome

In clinical trials, reactions consistent with serotonin syndrome were reported in patients treated with REYVOW who were not taking any other drugs associated with serotonin syndrome. Serotonin syndrome may also occur with REYVOW during coadministration with serotonergic drugs [e.g., selective serotonin reuptake inhibitors (SSRIs), serotonin norepinephrine reuptake inhibitors (SNRIs), tricyclic antidepressants (TCAs), and monoamine oxidase (MAO) inhibitors]. Serotonin syndrome symptoms may include mental status changes (e.g., agitation, hallucinations, coma), autonomic instability (e.g., tachycardia, labile blood pressure, hyperthermia), neuromuscular signs (e.g., hyperreflexia, incoordination), and/or gastrointestinal signs and symptoms (e.g., nausea, vomiting, diarrhea). The onset of symptoms usually occurs within minutes to hours of receiving a new or a greater dose of a serotonergic medication. Discontinue REYVOW if serotonin syndrome is suspected.

5.4 Medication Overuse Headache

Overuse of acute migraine drugs (e.g., ergotamines, triptans, opioids, or a combination of these drugs for 10 or more days per month) may lead to exacerbation of headache (i.e., medication overuse headache). Medication overuse headache may present as migraine-like daily headaches or as a marked increase in frequency of migraine attacks. Detoxification of patients including withdrawal of the overused drugs and treatment of withdrawal symptoms (which often includes a transient worsening of headache) may be necessary.

6 ADVERSE REACTIONS

The following clinically significant adverse reactions are described elsewhere in the labeling:

- Driving Impairment [see Warnings and Precautions (5.1)]
- Central Nervous System Depression [see Warnings and Precautions (5.2)]
- Serotonin Syndrome [see Warnings and Precautions (5.3)]
- Medication Overuse Headache [see Warnings and Precautions (5.4)]

6.1 Clinical Trials Experience

Because clinical studies are conducted under widely varying conditions, adverse reaction rates observed in the clinical studies of a drug cannot be directly compared to rates in the clinical studies of another drug and may not reflect the rates observed in practice.

The safety of REYVOW has been evaluated in 4,878 subjects who received at least one dose of REYVOW. In 2 placebo-controlled, Phase 3 trials in adult patients with migraine (Studies 1 and 2), a total of 3,177 patients received REYVOW 50, 100, or 200 mg [see Clinical Studies (14.1)]. Of the REYVOW-treated patients in these 2 studies, approximately 84% were female, 78% were White, 18% were Black, and 18% were of Hispanic or Latino ethnicity. The mean age at study entry was 42.4 years (range 18 to 81).

Long-term safety was assessed for 2,030 patients, dosing intermittently for up to 12 months in a long-term safety study. Of these, 728 patients were exposed to 100 mg or 200 mg for at least 3 months, 361 patients were exposed to these doses for at least 6 months, and 180 patients were exposed to these doses for at least 12 months, all of whom treated at least 2 migraine attacks per month on average. In that study, 14% (148 out of 1,039) in the 200 mg dose group, and 11% (112 out of 991) in the 100 mg dose group withdrew from the trial because of an adverse event. The most common adverse event resulting in discontinuation in the long-term safety study (greater than 2%) was dizziness.

Table 1 shows adverse reactions that occurred in at least 2% of patients treated with REYVOW and more frequently than in patients who received placebo in Studies 1 and 2. The most common adverse reactions (at least 5%) were dizziness, fatigue, paresthesia, and sedation.

Table 1: Adverse Reactions Occurring in ≥2% and at a Frequency Greater than Placebo in Studies 1 and 2
Adverse Reaction | REYVOW 50 mg N=654 % | REYVOW 100 mg N=1265 % | REYVOW 200 mg N=1258 % | Placebo N=1262 %
Dizziness | 9 | 15 | 17 | 3
Fatiguea | 4 | 5 | 6 | 1
Paresthesiab | 3 | 7 | 9 | 2
Sedationc | 6 | 6 | 7 | 2
Nausea and/or Vomiting | 3 | 4 | 4 | 2
Muscle Weakness | 1 | 1 | 2 | 0
a Fatigue includes the adverse reaction related terms asthenia and malaise.
b Paresthesia includes the adverse reaction related terms paresthesia oral, hypoesthesia, and hypoesthesia oral.
c Sedation includes the adverse reaction related term somnolence.

Less Common Adverse Reactions

The following adverse reactions occurred in less than 2% of REYVOW-treated patients but more frequently than in patients receiving placebo: vertigo, incoordination, lethargy, visual impairment, feeling abnormal, feeling hot or feeling cold, palpitations, anxiety, tremor, restlessness, sleep abnormalities including sleep disturbance and abnormal dreams, muscle spasm, limb discomfort, cognitive changes, confusion, euphoric mood, chest discomfort, speech abnormalities, dyspnea, and hallucinations.

Hypersensitivity

Events of hypersensitivity, including angioedema, rash and photosensitivity reaction, occurred in patients treated with REYVOW. In controlled trials, hypersensitivity was reported in 0.2% of patients treated with REYVOW compared to no patients who received placebo. If a serious or severe hypersensitivity reaction occurs, initiate appropriate therapy and discontinue administration of REYVOW.

Vital Sign Changes

Heart Rate Decrease

REYVOW was associated with mean decreases in heart rate of 5 to 10 beats per minute (bpm) while placebo was associated with mean decreases of 2 to 5 bpm. Consider evaluating heart rate after administration of REYVOW in patients for whom these changes may not be tolerated, including patients taking other medications that lower heart rate [see Drug Interactions (7.3)].

Blood Pressure Increase

REYVOW may increase blood pressure following a single dose. In non-elderly healthy volunteers there was a mean increase from baseline in ambulatory systolic and diastolic blood pressure of approximately 2 to 3 mm Hg one hour after administration of 200 mg REYVOW compared to a mean increase of up to 1 mm Hg for placebo. In healthy volunteers over 65 years of age, there was a mean increase from baseline in ambulatory systolic blood pressure of 7 mm Hg one hour after administration of 200 mg REYVOW compared to a mean increase of 4 mm Hg for placebo. By 2 hours, there were no increases in mean blood pressure with REYVOW compared to placebo. REYVOW has not been well studied in patients with ischemic heart disease. Consider evaluating blood pressure after administration of REYVOW in patients for whom these changes may not be tolerated.

7 DRUG INTERACTIONS

7.1 CNS Depressants

Concomitant administration of REYVOW and alcohol or other CNS depressant drugs has not been evaluated in clinical studies. Because of the potential of REYVOW to cause sedation, as well as other cognitive and/or neuropsychiatric adverse reactions, REYVOW should be used with caution if used in combination with alcohol or other CNS depressants [see Warnings and Precautions (5.2)].

7.2 Serotonergic Drugs

Concomitant administration of REYVOW and drugs (e.g., SSRIs, SNRIs, TCAs, MAO inhibitors, trazodone, etc.), over-the counter medications (e.g., dextromethorphan), or herbal supplements (e.g., St. John's Wort) that increase serotonin may increase the risk of serotonin syndrome [see Warnings and Precautions (5.3)]. Use REYVOW with caution in patients taking medications that increase serotonin.

7.3 Heart Rate Lowering Drugs

REYVOW has been associated with a lowering of heart rate [see Adverse Reactions (6.1)]. In a drug interaction study, addition of a single 200 mg dose of REYVOW to propranolol decreased heart rate by an additional 5 beats per minute compared to propranolol alone, for a mean maximum of 19 beats per minute. Use REYVOW with caution in patients taking concomitant medications that lower heart rate if this magnitude of heart rate decrease may pose a concern.

7.4 P-glycoprotein (P-gp) Transporter Substrates

Coadministration of REYVOW with P-gp substrates where a small change in substrate plasma concentration may lead to serious toxicities (e.g., digoxin) is not recommended [see Clinical Pharmacology (12.3)].

8 USE IN SPECIFIC POPULATIONS

8.1 Pregnancy

Pregnancy Exposure Registry

There is a pregnancy exposure registry that monitors pregnancy outcomes in women exposed to REYVOW during pregnancy. Healthcare providers are encouraged to register pregnant patients, or pregnant women may enroll themselves in the registry by calling 1-833-464-4724. To learn more please call or visit www.migrainepregnancyregistry.com.

Risk Summary

There are no adequate data on the developmental risk associated with the use of REYVOW in pregnant women. In animal studies, adverse effects on development (increased incidences of fetal abnormalities, increased embryofetal and offspring mortality, decreased fetal body weight) occurred at maternal exposures less than (rabbit) or greater than (rat) those observed clinically (see Data).

In the U.S. general population, the estimated background risk of major birth defects and of miscarriage in clinically recognized pregnancies is 2% to 4% and 15% to 20%, respectively. The estimated rates of major birth defects (2.2% to 2.9%) and miscarriage (17%) among deliveries to women with migraine are similar to rates reported in women without migraine.

Clinical Considerations

Disease-Associated Maternal and/or Embryo/Fetal Risk

Published data have suggested that women with migraine may be at increased risk for preeclampsia and gestational hypertension during pregnancy.

Data

Animal Data

Oral administration of lasmiditan (0, 100, 175, or 250 mg/kg/day) to pregnant rats throughout organogenesis resulted in increases in skeletal variations at the mid and high doses and reduced fetal body weight at the high dose. The high dose was associated with maternal toxicity. At the no-effect dose (100 mg/kg/day) for adverse effects on embryofetal development in rats, plasma exposure (AUC) was approximately 10 times that in humans at the MRHD.

Oral administration of lasmiditan (0, 50, 75, or 115 mg/kg/day) to pregnant rabbits throughout organogenesis resulted in malformations (skeletal and visceral), increases in skeletal variations and embryofetal mortality, and decreased fetal body weight at the highest dose tested, which was associated with maternal toxicity. Plasma exposure (AUC) at the no-effect dose (75 mg/kg/day) for adverse effects on embryofetal development in rabbits was less than that in humans at the MRHD.

Oral administration of lasmiditan (0, 100, 150, or 225 mg/kg/day) to rats throughout pregnancy and lactation resulted in increases in stillbirth and neonatal mortality at the highest dose tested, which was associated with maternal toxicity and delayed parturition. Plasma exposure (AUC) at the no-effect dose (150 mg/kg/day) for adverse effects on pre- and postnatal development was approximately 16 times that in humans at the MRHD.

8.2 Lactation

Risk Summary

There are no data on the presence of lasmiditan in human milk, the effects of lasmiditan on the breastfed infant, or the effects of lasmiditan on milk production. Excretion of lasmiditan and/or metabolites into milk, at levels approximately 3 times those in maternal plasma, was observed in lactating rats following oral administration of lasmiditan.

The developmental and health benefits of breastfeeding should be considered along with the mother's clinical need for REYVOW and any potential adverse effects on the breastfed infant from REYVOW or from the underlying maternal condition.

8.4 Pediatric Use

Safety and effectiveness in pediatric patients have not been established.

8.5 Geriatric Use

In controlled clinical trials, dizziness occurred more frequently in patients who were at least 65 years of age (19% for REYVOW, 2% for placebo) compared to patients who were less than 65 years of age (14% for REYVOW, 3% for placebo). A larger increase in systolic blood pressure also occurred in patients 65 years of age and older compared to patients who were less than 65 years of age [see Adverse Reactions (6.1)]. Clinical studies of REYVOW did not include sufficient numbers of subjects aged 65 and over to determine whether there is a difference in efficacy in these patients compared to younger subjects. However, in clinical pharmacology studies, no clinically relevant effect on exposure to REYVOW was observed in elderly subjects [see Clinical Pharmacology (12.3)]. In general, dose selection for an elderly patient should be cautious, usually starting at the low end of the dosing range, reflecting the greater frequency of decreased hepatic, renal, or cardiac function, and of concomitant disease or other drug therapy.

8.6 Hepatic Impairment

No dosage adjustment is needed for patients with mild or moderate hepatic impairment (Child-Pugh A or B). REYVOW has not been studied in patients with severe hepatic impairment (Child-Pugh C) and its use in these patients is not recommended.

9 DRUG ABUSE AND DEPENDENCE

9.1 Controlled Substance

REYVOW contains lasmiditan, a Schedule V controlled substance (CV).

9.2 Abuse

Abuse is the intentional, non-therapeutic use of a drug, even once, for its desirable psychological or physiological effects. In a human abuse potential (HAP) study in recreational poly-drug users (n=58), single oral therapeutic doses (100 and 200 mg) and a supratherapeutic dose (400 mg) of REYVOW were compared to alprazolam (2 mg) (C-IV) and placebo. With all doses of REYVOW, subjects reported statistically significantly higher “drug liking” scores than placebo, indicating that REYVOW has abuse potential. In comparison to alprazolam, subjects who received REYVOW reported statistically significantly lower “drug liking” scores. In the HAP study, euphoric mood occurred to a similar extent with REYVOW 200 mg, REYVOW 400 mg, and alprazolam 2 mg (43-49%). A feeling of relaxation was noted in more subjects on alprazolam (22.6%) than with any dose of REYVOW (7-11%).

Phase 2 and 3 studies indicate that, at therapeutic doses, REYVOW produced adverse events of euphoria and hallucinations to a greater extent than placebo. However these events occur at a low frequency (about 1% of patients).

Evaluate patients for risk of drug abuse and observe them for signs of lasmiditan misuse or abuse.

9.3 Dependence

Physical withdrawal was not observed in healthy subjects following abrupt cessation after 7 daily doses of lasmiditan 200 mg or 400 mg.

11 DESCRIPTION

REYVOW (lasmiditan) is a serotonin (5-HT) 1F receptor agonist for oral administration. The chemical name of lasmiditan hemisuccinate is 2,4,6-trifluoro-N-[6-(1-methylpiperidine-4-carbonyl)pyridine-2-yl]benzamide hemisuccinate. It has the empirical formula of C19H18F3N3O2•0.5[C4H6O4] and a molecular weight of 436.41 (hemisuccinate). Lasmiditan hemisuccinate has the following structural formula:

Lasmiditan hemisuccinate is a white, crystalline powder that is sparingly soluble in water, slightly soluble in ethanol, and soluble in methanol. A 1 mg/mL aqueous solution of lasmiditan hemisuccinate has a pH of 6.8 at ambient conditions.

REYVOW 50 mg tablets contain 50 mg lasmiditan (equivalent to 57.824 mg lasmiditan hemisuccinate) and the inactive ingredients as follows:

Excipients – croscarmellose sodium, magnesium stearate, microcrystalline cellulose, pregelatinized starch, sodium lauryl sulfate.

Color mixture ingredients – black ferric oxide, polyethylene glycol, polyvinyl alcohol, talc, titanium dioxide.

REYVOW 100 mg tablets contain 100 mg lasmiditan (equivalent to 115.65 mg lasmiditan hemisuccinate) and the inactive ingredients as follows:

Excipients – croscarmellose sodium, magnesium stearate, microcrystalline cellulose, pregelatinized starch, sodium lauryl sulfate.

Color mixture ingredients – black ferric oxide, polyethylene glycol, polyvinyl alcohol, red ferric oxide, talc, titanium dioxide.

12 CLINICAL PHARMACOLOGY

12.1 Mechanism of Action

Lasmiditan binds with high affinity to the 5-HT1F receptor. Lasmiditan presumably exerts its therapeutic effects in the treatment of migraine through agonist effects at the 5-HT1F receptor; however, the precise mechanism is unknown.

12.2 Pharmacodynamics

Cardiac Electrophysiology

At a dose two times the maximum recommended daily dose, REYVOW does not prolong the QTc interval to any clinically relevant extent.

12.3 Pharmacokinetics

Absorption

Following oral administration, lasmiditan is rapidly absorbed with a median tmax of 1.8 hours. In patients with migraine, the absorption or pharmacokinetics of lasmiditan was not different during a migraine attack versus during the interictal period.

Effect of Food

Coadministration of lasmiditan with a high-fat meal increased the mean lasmiditan Cmax and AUC values by 22% and 19%, respectively, and delayed the median tmax by 1 hour. This difference in exposure is not expected to be clinically significant [see Dosage and Administration (2)]. Lasmiditan was administered without regard to food in clinical efficacy studies.

Distribution

The human plasma protein binding of lasmiditan is approximately 55% to 60% and independent of concentration between 15 and 500 ng/mL.

Elimination

Lasmiditan was eliminated with a geometric mean t½ value of approximately 5.7 hours. No accumulation of lasmiditan was observed with daily dosing. Lasmiditan is primarily eliminated via metabolism, with ketone reduction representing the major pathway. Renal excretion is a minor route of lasmiditan clearance.

Metabolism

Lasmiditan undergoes hepatic and extrahepatic metabolism primarily by non-CYP enzymes. The following enzymes are not involved in metabolism of lasmiditan: MAO-A, MAO-B, flavin monooxygenase 3, CYP450 reductase, xanthine oxidase, alcohol dehydrogenase, aldehyde dehydrogenase, and aldo-keto reductases. Lasmiditan is also metabolized to M7 (oxidation on piperidine ring) and M18 (combination of M7 and M8 pathways). These metabolites are considered pharmacologically inactive.

Excretion

Recovery of unchanged lasmiditan in urine was low and accounted for approximately 3% of the dose. Metabolite S-M8 represented approximately 66% of the dose in urine, with the majority of recovery within 48 hours postdose.

Specific Populations

Age, Sex, Race/Ethnicity, and Body Weight

Based on a population pharmacokinetic (PK) analysis, age, sex, race/ethnicity, and body weight did not have a significant effect on the PK (Cmax and AUC) of lasmiditan. Therefore, no dose adjustments are warranted based on age, sex, race/ethnicity, or body weight.

Geriatric Use

In a clinical pharmacology study, administration of lasmiditan to subjects 65 years of age or older demonstrated 26% greater exposure in AUC(0-∞) and 21% higher Cmax, compared to subjects 45 years of age or less. This difference in exposure is not expected to be clinically significant [see Use in Specific Populations (8.5)].

Renal Impairment

In a clinical pharmacology study, administration of lasmiditan to subjects with severe renal impairment (eGFR <30 mL/min/1.73 m^2) demonstrated 18% greater exposure in AUC(0-∞) and 13% higher Cmax, compared to subjects with normal renal function. No dose adjustment is required based on renal function.

Hepatic Impairment

In a clinical pharmacology study, subjects with mild and moderate hepatic impairment (Child-Pugh Class A and B, respectively) demonstrated 11% and 35%, respectively, greater exposure [AUC(0-∞)] to lasmiditan, compared to subjects with normal hepatic function. The Cmax were higher by 19% and 33%, respectively, for subjects with mild and moderate hepatic impairment. This difference in exposure is not expected to be clinically significant. The use of lasmiditan has not been studied in subjects with severe hepatic impairment [see Use in Specific Populations (8.6)].

Drug Interaction Studies

Potential for Lasmiditan to Affect Other Drugs

Drug Metabolizing Enzymes

Lasmiditan is an in-vitro inhibitor of CYP2D6 but did not significantly inhibit the activity of other CYP450 enzymes. Modeling and simulation of the impact of lasmiditan on the exposure of dextromethorphan, a recognized sensitive CYP2D6 substrate, indicate that lasmiditan is unlikely to exert clinically significant inhibition of CYP2D6. Lasmiditan, M7, S-M8, and [S,R]-M18 are not reversible or time-dependent inhibitors of monoamine oxidase A (MAO-A).

Daily dosing of lasmiditan did not alter the PK of midazolam, caffeine, or tolbutamide, which are substrates of CYP3A, CYP1A2, and CYP2C9, respectively. Coadministration of lasmiditan with sumatriptan, propranolol, or topiramate resulted in no clinically meaningful changes in exposure of these medicinal products.

Drug Transporters

In a drug interaction study in healthy volunteers, co-administration of 200 mg REYVOW with dabigatran (P-gp substrate) increased the systemic exposures, AUC and Cmax, of dabigatran by 25% and 22%, respectively [see Drug Interactions (7.4)]. Co-administration of 200 mg REYVOW with rosuvastatin (BCRP substrate) did not affect exposures of rosuvastatin.

Lasmiditan inhibits OCT1 in-vitro. However, in a drug-drug interaction study with lasmiditan and sumatriptan (OCT1 substrate), no change in sumatriptan PK was observed. Lasmiditan inhibits renal efflux transporters, MATE1 and MATE2-K, in-vitro.

Potential for Other Drugs to Affect Lasmiditan

Drug Metabolizing Enzymes

Lasmiditan undergoes hepatic and extrahepatic metabolism primarily by non-CYP enzymes. Therefore, it is unlikely that CYP inhibitors or inducers will affect lasmiditan pharmacokinetics. Clinical studies of lasmiditan with sumatriptan, propranolol, or topiramate did not show any significant drug interaction potential.

Drug Transporters

Lasmiditan is a substrate for P-gp in-vitro.

13 NONCLINICAL TOXICOLOGY

13.1 Carcinogenesis, Mutagenesis, Impairment of Fertility

Carcinogenesis

No drug-related tumors were observed following oral administration of lasmiditan to TgRasH2 mice at doses of up to 150 (males) or 250 (females) mg/kg/day for 26 weeks or to rats at doses of up to 75 mg/kg/day for 2 years. Plasma exposures (AUC) at the highest dose tested in rats were approximately 15 times that in humans at the maximum recommended human dose (MRHD) of 200 mg/day.

Mutagenesis

Lasmiditan was negative in in vitro (bacterial reverse mutation, chromosomal aberration in mammalian cells) and in vivo (mouse bone marrow micronucleus) assays.

Impairment of Fertility

Oral administration of lasmiditan to male (0, 100, 175, or 200 mg/kg/day) or female (0, 100, 150, or 200 mg/kg/day) rats prior to and during mating and continuing in females to Gestation Day 7 resulted in no adverse effects on fertility or reproductive performance. Plasma exposures (AUC) at the highest dose tested (200 mg/kg/day) were approximately 26 times that in humans at the MRHD.

14 CLINICAL STUDIES

14.1 Migraine

The efficacy of REYVOW in the acute treatment of migraine was demonstrated in two randomized, double-blind, placebo-controlled trials [Study 1 (NCT02439320) and Study 2 (NCT02605174)]. These studies enrolled patients with a history of migraine with and without aura according to the International Classification of Headache Disorders (ICHD-II) diagnostic criteria. Patients were predominantly female (84%), and White (78%), with a mean age of 42 years (range 18-81). Twenty-two percent of patients were taking preventive medication for migraine at baseline. Study 1 randomized patients to REYVOW 100 mg (n=744), or 200 mg (n=745) or placebo (n=742) and Study 2 randomized patients to REYVOW 50 mg (n=750), 100 mg (n=754), or 200 mg (n=750) or placebo (n=751). Patients were allowed to take a rescue medication 2 hours after taking study drug; however, opioids, barbiturates, triptans, and ergots were not allowed within 24 hours of study drug administration.

The primary efficacy analyses were conducted in patients that treated a migraine with moderate to severe pain within 4 hours of the onset of the attack. The efficacy of REYVOW was established by an effect on pain freedom at 2 hours and Most Bothersome Symptom (MBS) freedom at 2 hours compared to placebo for Studies 1 and 2. Pain freedom was defined as a reduction of moderate or severe headache pain to no pain, and MBS freedom was defined as the absence of the self-identified MBS (photophobia, phonophobia, or nausea). Among patients who selected an MBS, the most commonly selected MBS was photophobia (54%), followed by nausea (24%), and phonophobia (22%).

In both studies, the percentage of patients achieving pain freedom and MBS freedom 2 hours after treatment was significantly greater among patients receiving REYVOW at all doses compared to those receiving placebo (see Table 2).

Table 2: Migraine Efficacy Endpoints after Treatment for Studies 1 and 2
 | Study 1 |  |  | Study 2
 | REYVOW 100 mg | REYVOW 200 mg | Placebo | REYVOW 50 mg | REYVOW 100 mg | REYVOW 200 mg | Placebo
Pain Free at 2 hours
N | 498 | 503 | 515 | 544 | 523 | 521 | 534
% Responders | 28.3 | 31.8 | 15.3 | 28.3 | 31.4 | 38.8 | 21.0
Difference from placebo (%) | 13 | 16.5 |  | 7.3 | 10.4 | 17.8
p-value | <0.001 | <0.001 |  | 0.006 | <0.001 | <0.001
MBS Free at 2 hours
N | 464 | 467 | 480 | 502 | 491 | 478 | 509
% Responders | 41.2 | 40.7 | 29.6 | 40.8 | 44.0 | 48.7 | 33.2
Difference from placebo (%) | 11.6 | 11.1 |  | 7.6 | 10.8 | 15.5
p-value | <0.001 | <0.001 |  | 0.014 | <0.001 | <0.001

Pain relief at 2 hours, defined as a reduction in migraine pain from moderate or severe to mild or none, was also evaluated (see Table 3).

Table 3: Additional Migraine Efficacy Endpoint after Treatment for Studies 1 and 2
 | Study 1 |  |  | Study 2
 | REYVOW 100 mg | REYVOW 200 mg | Placebo | REYVOW 50 mg | REYVOW 100 mg | REYVOW 200 mg | Placebo
Pain Relief at 2 hoursa
N | 498 | 503 | 515 | 544 | 523 | 521 | 534
% Responders | 54.0 | 55.3 | 40.0 | 55.9 | 61.4 | 61.0 | 45.1
Difference from placebo (%) | 14.0 | 15.3 |  | 10.8 | 16.3 | 15.9
a The analysis of pain relief was descriptive and was not controlled for Type I error.

Figure 1 presents the percentage of patients achieving migraine pain freedom within 2 hours following treatment in Studies 1 and 2.

Figure 1: Percentage of Patients Achieving Migraine Pain Freedom within 2 Hours in Pooled Studies 1 and 2

a The 50 mg arm was only included in Study 2.

Figure 2 presents the percentage of patients achieving MBS freedom within 2 hours in Studies 1 and 2.

Figure 2: Percentage of Patients Achieving MBS Freedom within 2 Hours in Pooled Studies 1 and 2

a The 50 mg arm was only included in Study 2.

14.2 Effects on Driving

Driving performance was assessed at 90 minutes after administration of REYVOW 50 mg, 100 mg, 200 mg, alprazolam 1 mg, and placebo in a randomized, double-blind, placebo- and active-controlled, five-period crossover study in 90 healthy volunteers (mean age 34.9 years) using a computer-based driving simulation. Driving performance was evaluated using a validated threshold established in a population with blood alcohol concentration of 0.05%. The primary outcome measure was the difference from placebo in the Standard Deviation of Lateral Position (SDLP), a measure of driving performance. A dose-dependent impairment of computer-based simulated driving performance was seen with all doses of REYVOW at 90 minutes after administration.

Driving performance was also assessed at 8, 12, and 24 hours after administration of REYVOW 100 mg or 200 mg, in a separate randomized, double-blind, placebo- and active-controlled, four-period crossover study in 67 healthy volunteers (mean age 32.8 years) evaluating computer-based simulated driving performance using SDLP as the primary endpoint. Diphenhydramine 50 mg was used as a positive control. The mean SDLP did not reach the threshold for driving impairment at 8 hours or later after administration of REYVOW 100 or 200 mg.

16 HOW SUPPLIED/STORAGE AND HANDLING

16.1 How Supplied

REYVOW (lasmiditan) 50 mg tablets are light gray, oval, film coated, tablets with “L-50” debossed on one side and “4312” on the other.

REYVOW (lasmiditan) 100 mg tablets are light purple, oval, film coated, tablets with “L-100” debossed on one side and “4491” on the other.

 | Strengths
 | 50 mg | 100 mg
Tablet color | Light gray | Light purple
Imprint (debossed) | L-50 4312 | L-100 4491
Carton of 8 | NDC 0002-4312-08 | NDC 0002-4491-08

16.2 Storage and Handling

Store at 20°C to 25°C (68°F to 77°F); excursions permitted to 15°C to 30°C (59°F to 86°F) [see USP Controlled Room Temperature].

17 PATIENT COUNSELING INFORMATION

Advise the patient to read the FDA-approved patient labeling (Medication Guide).

Driving Impairment – Advise patients not to engage in potentially hazardous activities requiring complete mental alertness, such as driving a motor vehicle or operating machinery for at least 8 hours after taking each dose of REYVOW. Patients who cannot follow this advice should not take REYVOW. Patients may not be able to assess their own driving competence and the degree of impairment caused by REYVOW [see Warnings and Precautions (5.1)].

CNS Depression – Inform patients that REYVOW may cause dizziness and sedation. Advise patients to use caution if taking REYVOW in combination with alcohol or other CNS depressants [see Warnings and Precautions (5.2) and Drug Interactions (7.1)].

Serotonin Syndrome – Caution patients about the risk of serotonin syndrome with the use of REYVOW, particularly during combined use with serotonergic medications such as SSRIs, SNRIs, TCAs, or MAO inhibitors [see Warnings and Precautions (5.3) and Drug Interactions (7.2)].

Medication Overuse Headache – Inform patients that use of drugs to treat migraine attacks for 10 or more days per month may lead to an exacerbation of headache, and encourage patients to record headache frequency and drug use (e.g., by keeping a headache diary) [see Warnings and Precautions (5.4)].

Hypersensitivity – Advise patients to seek immediate medical attention if they experience any symptoms of serious or severe hypersensitivity reaction [see Adverse Reactions (6.1)].

Abuse and Dependence – Advise patients that REYVOW is a federally controlled substance because it has the potential to be abused [see Drug Abuse and Dependence (9)]. Advise patients to keep their medication secure.

Pregnancy

- Advise patients to notify their healthcare provider if they become pregnant during treatment or plan to become pregnant [see Use in Specific Populations (8.1)].
- Advise patients that there is a pregnancy exposure registry that monitors pregnancy outcomes in women exposed to REYVOW during pregnancy [see Use in Specific Populations (8.1)].

Nursing Mothers – Inform patients to notify their healthcare provider if they are breastfeeding or plan to breastfeed [see Use in Specific Populations (8.2)].

Administration – Advise patients to swallow tablets whole (do not split, crush, or chew) [see Dosage and Administration (2)].

Literature revised September 2022

Marketed by: Lilly USA, LLC, Indianapolis, IN 46285, USA
Copyright © 2019, 2022, Eli Lilly and Company. All rights reserved.

REY-0007-USPI-20220915

Medication Guide
REYVOW® (RAY-vow)
(lasmiditan)
tablets, for oral use, CV

What is the most important information I should know about REYVOW?

- Do not drive or operate machinery for at least 8 hours after you take REYVOW, even if you feel well enough.
- You should not take REYVOW if you cannot wait at least 8 hours between taking REYVOW and driving or operating machinery.

What is REYVOW?
REYVOW is a prescription medicine used for the acute treatment of migraine attacks with or without aura in adults.

- REYVOW is not used as a preventive treatment of migraine.
- It is not known if REYVOW is safe and effective in children.
- REYVOW is a federally controlled substance (CV) because it contains lasmiditan that can be abused. Keep REYVOW in a safe place to protect it from theft. Never give your REYVOW to anyone else, because it may harm them. Selling or giving away REYVOW is against the law. Tell your healthcare provider if you have ever abused or been dependent on alcohol, prescription medicines or street drugs.

Before you take REYVOW, tell your healthcare provider about all of your medical conditions, including if you:

- have liver problems
- have high blood pressure
- have a low heart rate
- are allergic to lasmiditan
- are pregnant or plan to become pregnant. It is not known if REYVOW will harm your unborn baby.
  - Pregnancy Registry: There is a pregnancy registry for pregnant women who take REYVOW. The purpose of this registry is to collect information about the health of you and your baby if you take REYVOW during pregnancy. To learn more call 1-833-464-4724 or visit www.migrainepregnancyregistry.com. You may also talk to your healthcare provider about how you can take part in this registry.
- are breastfeeding or plan to breastfeed. It is not known if REYVOW passes into your breastmilk.

Tell your healthcare provider about all the medicines you take, including prescription and over-the-counter medicines, vitamins, and herbal supplements. Your healthcare provider will decide if you can take REYVOW with your other medicines.
Especially, tell your healthcare provider if you take:

- propranolol or other medicines that can lower your heart rate
- any medicines that can increase your blood pressure
- any medicines that make you sleepy
- anti-depressant medicines called:
  - selective serotonin reuptake inhibitors (SSRIs)
  - serotonin norepinephrine reuptake inhibitors (SNRIs)
  - tricyclic anti-depressants (TCAs)
  - monoamine oxidase inhibitors (MAOIs)

Ask your healthcare provider or pharmacist for a list of these medicines if you are not sure.
Know the medicines you take. Keep a list of them and show it to your healthcare provider or pharmacist when you get a new medicine.

How should I take REYVOW?

- Take REYVOW exactly as your healthcare provider tells you to take it.
- Your healthcare provider may change your dose. Do not change your dose without first talking to your healthcare provider.
- Take REYVOW tablets by mouth with or without food.
- Swallow REYVOW tablets whole. Do not split, crush, or chew.
- Do not take more than one dose in a 24-hour period.
  - If you take REYVOW 50 mg, 100 mg, or 200 mg, and your headache goes away but comes back, you should not take a second dose within 24 hours.
- Some people who take too many REYVOW tablets may have worse headaches (medication overuse headache). If your headaches get worse, your healthcare provider may decide to stop your treatment with REYVOW.
- You should write down when you have headaches and when you take REYVOW so you can talk to your healthcare provider about how REYVOW is working for you.

What should I avoid while taking REYVOW?

- Do not drive or operate machinery for at least 8 hours after taking REYVOW.
- You should not drink alcohol or take other medicines that make you drowsy while taking REYVOW.

What are the possible side effects of REYVOW?
REYVOW can cause serious side effects including:

- See “What is the most important information I should know about REYVOW?”
  - serotonin syndrome. Serotonin syndrome is a rare but serious problem that can happen in people using REYVOW, especially if REYVOW is used with anti-depressant medicines called SSRIs or SNRIs. Call your healthcare provider right away if you have any of the following symptoms of serotonin syndrome:
    - mental changes such as seeing things that are not there (hallucinations), agitation, or coma
    - fast heartbeat
    - changes in blood pressure
    - high body temperature
    - tight muscles
    - trouble walking
    - nausea, vomiting, or diarrhea
  - medication overuse headache. Some people who take medicines like REYVOW for the acute treatment of migraine attacks for 10 or more days each month may have worse headaches (medication overuse headache). If your headaches get worse, your healthcare provider may decide to stop your treatment with REYVOW.

The most common side effects of REYVOW include:

- dizziness
- sleepiness

- numbness
- feeling tired

- tingling

Tell your healthcare provider if you have any side effect that bothers you or that does not go away.
These are not all of the possible side effects of REYVOW. For more information ask your healthcare provider or pharmacist.
Call your doctor for medical advice about side effects. You may report side effects to FDA at 1-800-FDA-1088. You may also report side effects to Lilly at 1-800-LillyRx (1-800-545-5979).

How should I store REYVOW?

- Store REYVOW at room temperature between 68°F to 77°F (20°C to 25°C).
- Keep REYVOW and all medicines out of the reach of children.

General information about the safe and effective use of REYVOW.
Medicines are sometimes prescribed for purposes other than those listed in a Medication Guide. Do not use REYVOW for a condition for which it was not prescribed. Do not give REYVOW to other people, even if they have the same symptoms you have. It may harm them.
You can ask your pharmacist or healthcare provider for information about REYVOW that is written for health professionals.

What are the ingredients in REYVOW?
Active ingredient: lasmiditan hemisuccinate
Inactive ingredients: croscarmellose sodium, magnesium stearate, microcrystalline cellulose, pregelatinized starch, sodium lauryl sulfate.
Color mixture ingredients: black ferric oxide, polyethylene glycol, polyvinyl alcohol, talc, titanium dioxide. 100 mg tablets also contain red ferric oxide.
REYVOW is a registered trademark of Eli Lilly and Company.
Marketed by: Lilly USA, LLC, Indianapolis, IN 46285, USA
www.REYVOW.com
Copyright © 2019, 2022, Eli Lilly and Company. All rights reserved.
For more information go to www.REYVOW.com or call 1-800-LillyRx (1-800-545-5979).

This Medication Guide has been approved by the U.S. Food and Drug Administration

Revised: 07/2022

REY-0005-MG-20220715

PACKAGE LABEL - REYVOW 50 mg 8ct carton

NDC 0002-4312-08

8 tablets (2 cards of 4 tablets)

REYVOW®

(lasmiditan) CV

tablets 50 mg

Each tablet contains 50 mg of lasmiditan.

Rx only

www.REYVOW.com

50 mg

Dispense enclosed Medication Guide to each patient.

Lilly

PACKAGE LABEL - REYVOW 100 mg 8ct carton

NDC 0002-4491-08

8 tablets (2 cards of 4 tablets)

REYVOW®

(lasmiditan) CV

tablets 100 mg

Each tablet contains 100 mg of lasmiditan.

Rx only

www.REYVOW.com

100 mg

Dispense enclosed Medication Guide to each patient.

Lilly